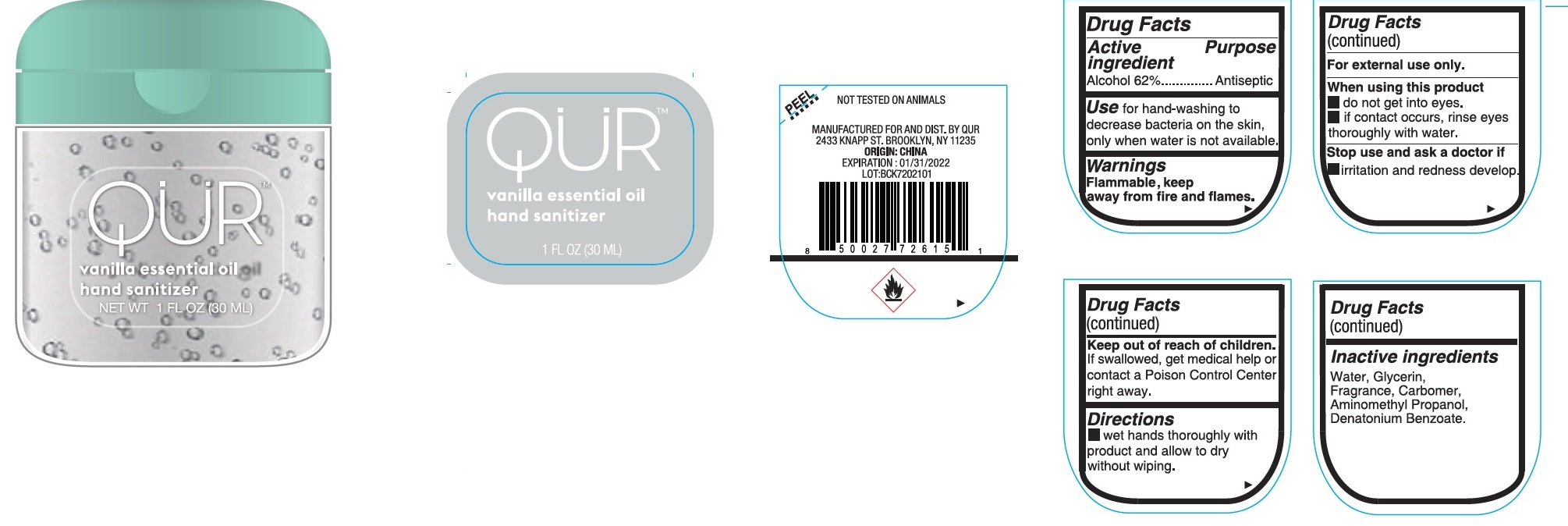 DRUG LABEL: QUR Vanilla essential oil hand sanitizer
NDC: 81761-112 | Form: GEL
Manufacturer: Qur, Inc
Category: otc | Type: HUMAN OTC DRUG LABEL
Date: 20231026

ACTIVE INGREDIENTS: ALCOHOL 62 mL/100 mL
INACTIVE INGREDIENTS: WATER; CARBOMER HOMOPOLYMER, UNSPECIFIED TYPE; AMINOMETHYLPROPANOL; DENATONIUM BENZOATE; GLYCERIN

QUR Vanilla essential oil hand sanitizer

Active ingredient

Alcohol 62%

Purpose

Antiseptic

Use

for hand-washing to decrease bacteria on the skin, only when water is not available.

Warnings

Flammable, keep away from fire and flames.

For external use only.

When using this product

- do not get into eyes.
- if contact occurs, rinse eyes thoroughly with water.

Stop use and ask a doctor if

- irritation and redness develop.

Keep out of the reach of children.

If swallowed, get medical help or contact a Poison Control Center right away.

Directions

- wet hands thoroughly with product and allow to dry without wiping.

Inactive ingredients

Water, Glycerin, Fragrance, Carbomer, Aminomethyl Propanol, Denatonium Benzoate.